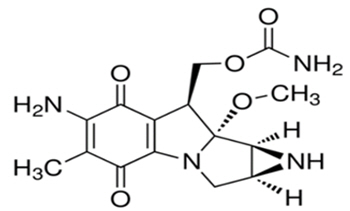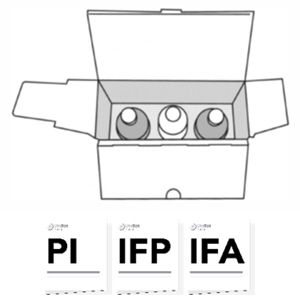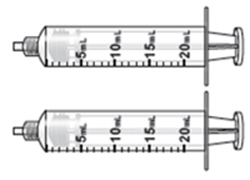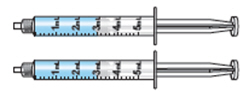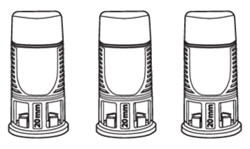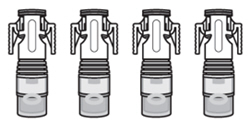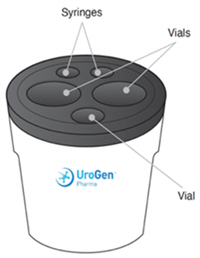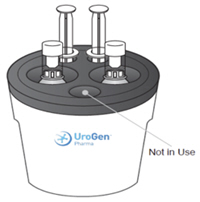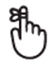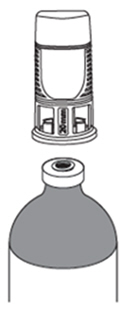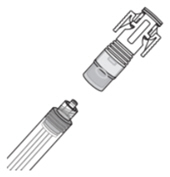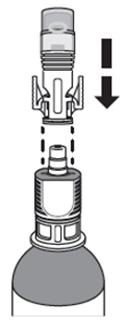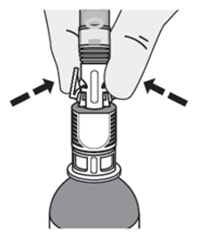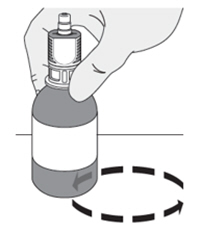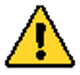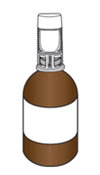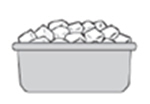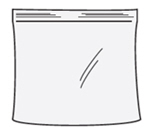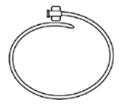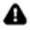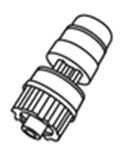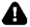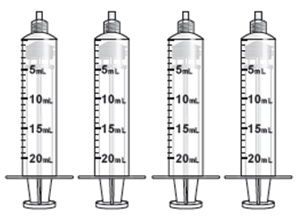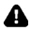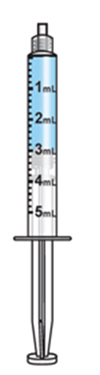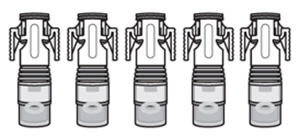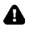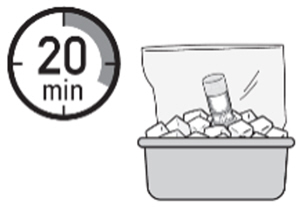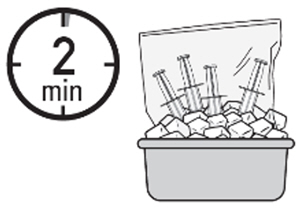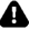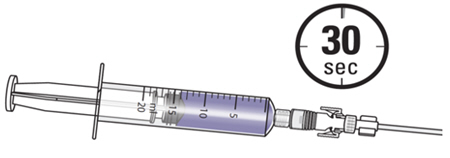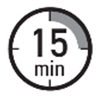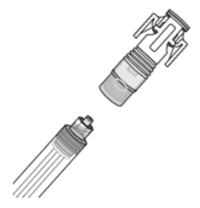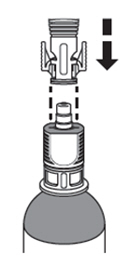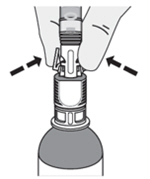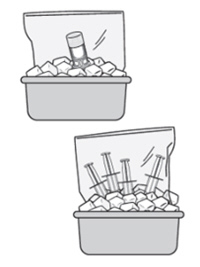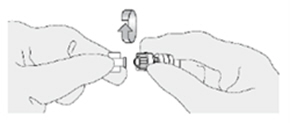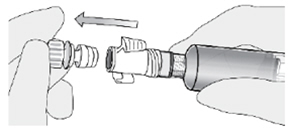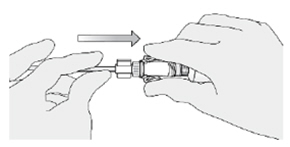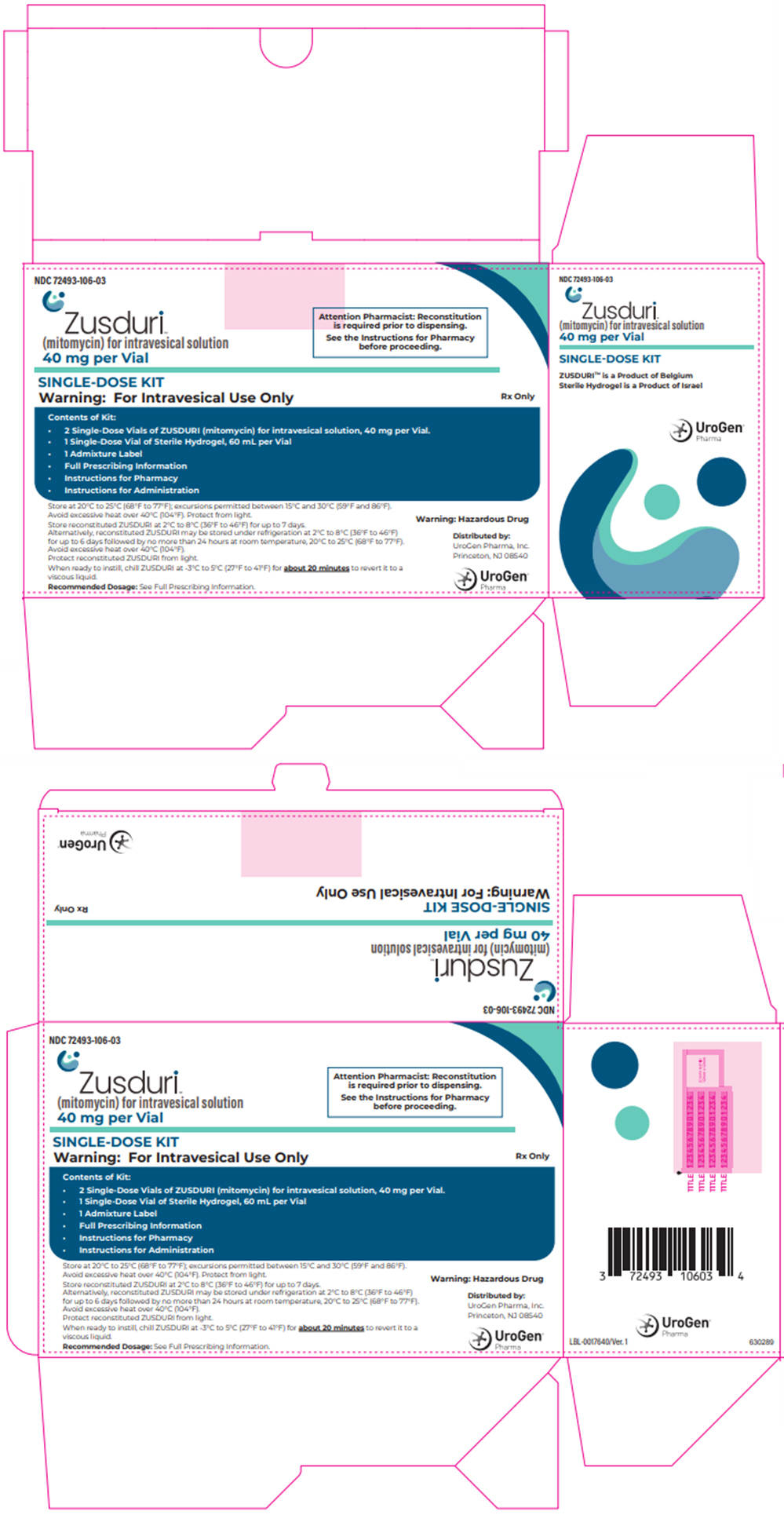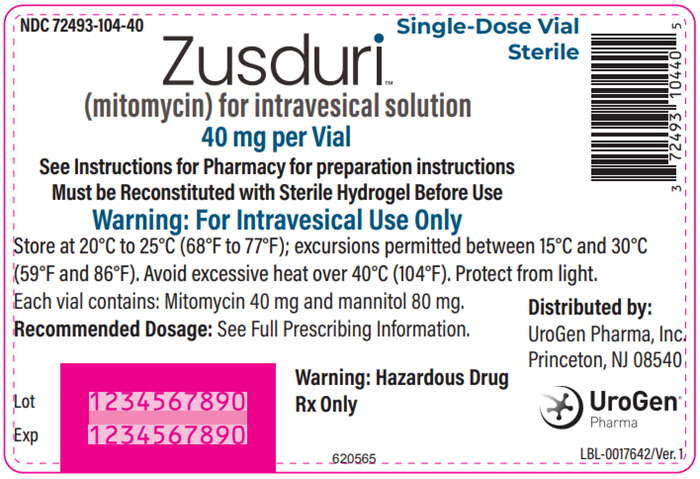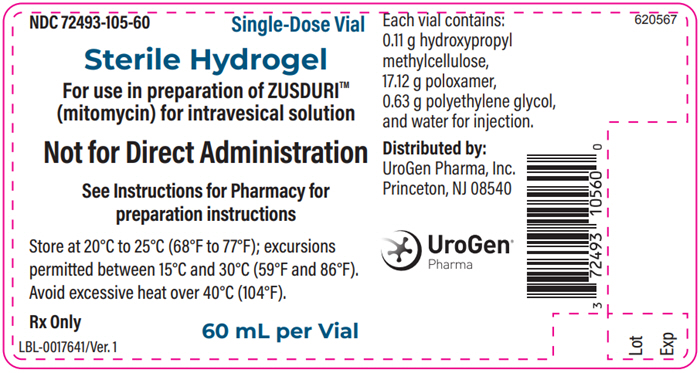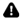 DRUG LABEL: ZUSDURI
NDC: 72493-106 | Form: KIT | Route: INTRAVESICAL
Manufacturer: UroGen Pharma, Inc
Category: prescription | Type: HUMAN PRESCRIPTION DRUG LABEL
Date: 20250620

ACTIVE INGREDIENTS: Mitomycin 40 mg/1 1
INACTIVE INGREDIENTS: Mannitol; POLOXAMER 407; POLYETHYLENE GLYCOL, UNSPECIFIED; HYPROMELLOSE, UNSPECIFIED; WATER

HIGHLIGHTS OF PRESCRIBING INFORMATION

These highlights do not include all the information needed to use ZUSDURI safely and effectively. See full prescribing information for ZUSDURI.
ZUSDURI™ (mitomycin) for intravesical solution
Initial U.S. Approval: 1974

1 INDICATIONS AND USAGE

ZUSDURI is an alkylating drug indicated for the treatment of adult patients with recurrent low-grade intermediate-risk non-muscle invasive bladder cancer (LG-IR-NMIBC). (1)

2 DOSAGE AND ADMINISTRATION

- Administer ZUSDURI by intravesical instillation only. Do not administer by pyelocalyceal instillation or by any other route. (2.1)
- The recommended dose of ZUSDURI is 75 mg (56 mL) instilled once weekly for six weeks. (2.2)

3 DOSAGE FORMS AND STRENGTHS

For intravesical solution: A kit containing the following:

- Two 40 mg (each) single-dose vials of mitomycin for intravesical solution. (3)
- One vial of 60 mL sterile hydrogel for reconstitution. (3)

4 CONTRAINDICATIONS

- Perforation of the bladder, (4)
- Prior hypersensitivity reaction to mitomycin or any component of the product. (4)

5 WARNINGS AND PRECAUTIONS

- Risks in Patients with Perforated Bladder: Evaluate the bladder before the intravesical instillation of ZUSDURI. Do not administer to patients with a perforated bladder or in whom the integrity of the bladder mucosa has been compromised. (4, 5.1).
- Embryo-Fetal Toxicity: Can cause fetal harm. Advise of potential risk to a fetus and to use effective contraception. (5.2, 8.1, 8.3)

6 ADVERSE REACTIONS

The most common (≥ 10%) adverse reactions, including laboratory abnormalities, that occurred in patients were increased creatinine, increased potassium, dysuria, decreased hemoglobin, increased aspartate aminotransferase, increased alanine aminotransferase, increased eosinophils, decreased lymphocytes, urinary tract infection, decreased neutrophils, and hematuria. (6.1)

To report SUSPECTED ADVERSE REACTIONS, contact UroGen Pharma at 1-855-987-6436 or FDA at 1-800-FDA-1088 or www.fda.gov/medwatch.

8 USE IN SPECIFIC POPULATIONS

Lactation: Advise not to breastfeed. (8.2)

FULL PRESCRIBING INFORMATION

1 INDICATIONS AND USAGE

ZUSDURI™ is indicated for the treatment of adult patients with recurrent low-grade intermediate-risk non-muscle invasive bladder cancer (LG-IR-NMIBC).

2 DOSAGE AND ADMINISTRATION

2.1 Important Administration Instructions

Administer ZUSDURI by intravesical instillation only. Do not administer by pyelocalyceal instillation or by any other route.

2.2 Recommended Dose

The recommended dose of ZUSDURI is 75 mg (56 mL) instilled once weekly for six weeks into the bladder via a urinary catheter. [see Dosage and Administration (2.4)]

2.3 Preparation Instructions

See the Instructions for Pharmacy enclosed in the carton for complete information on preparation.

ZUSDURI must be reconstituted with sterile hydrogel under chilled conditions. Reconstituted ZUSDURI has reverse thermal properties with a gelation point of approximately 19°C (66°F) and will appear as a viscous liquid under chilled conditions and a semisolid gel at room temperature.

Storage Instructions for Reconstituted ZUSDURI:

- Instill reconstituted ZUSDURI as soon as possible.
- If not used immediately, store reconstituted ZUSDURI:
  - under refrigeration at 2℃ to 8℃ (36°F to 46°F) for up to 7 days; or
  - under refrigeration at 2℃ to 8℃ (36°F to 46°F) for up to 6 days followed by no more than 24 hours at room temperature, 20°C to 25°C (68°F to 77°F).
- Discard 7 days after reconstitution.
- Protect from light.
- Avoid excessive heat over 40°C (104°F).

ZUSDURI is a hazardous drug. Follow applicable special handling and disposal procedures.^1

2.4 Bladder Instillation of ZUSDURI

See the Instructions for Administration enclosed in the carton for complete information on bladder instillation.

ZUSDURI must be chilled at -3°C to 5°C (27°F to 41°F) to convert to a viscous liquid prior to instillation. When instilling ZUSDURI, each syringe must be emptied within thirty (30) seconds to avoid gelation.

Instillation of ZUSDURI requires syringes and a urinary catheter with fixed Luer Lock connectors.

Advise patients that ZUSDURI may discolor urine to a violet to blue color following the instillation procedure. Advise patients for at least 24 hours post-instillation to avoid urine contact with skin, to void urine sitting on a toilet, to wash hands and genital area with water and soap after each urination, and to flush the toilet several times after use.

3 DOSAGE FORMS AND STRENGTHS

For intravesical solution: A kit containing the following:

- Two 40 mg (each) single-dose vials of sterile, lyophilized, grey to greyish-purple, cake or powder of mitomycin for intravesical solution.
- One single-dose vial of 60 mL of sterile, clear, colorless gel with or without bubbles at room temperature or clear, colorless liquid at 2°C to 8°C (36°F to 46°F), to be used as a vehicle for reconstitution.

4 CONTRAINDICATIONS

ZUSDURI is contraindicated in patients with:

- Perforation of the bladder [see Warnings and Precautions (5.1)],
- Prior hypersensitivity reactions to mitomycin or any component of the product.

5 WARNINGS AND PRECAUTIONS

5.1 Risks in Patients with Perforated Bladder

ZUSDURI may lead to systemic exposure to mitomycin and severe adverse reactions if administered to patients with a perforated bladder or to those in whom the integrity of the bladder mucosa has been compromised.

Evaluate the bladder before the intravesical instillation of ZUSDURI and do not administer to patients with a perforated bladder or mucosal compromise until bladder integrity has been restored [see Contraindications (4)].

5.2 Embryo-Fetal Toxicity

Based on findings in animals and mechanism of action, ZUSDURI can cause fetal harm when administered to a pregnant woman. In animal reproduction studies, administration of mitomycin resulted in teratogenicity. Advise females of reproductive potential to use effective contraception during treatment with ZUSDURI and for 6 months following the last dose. Advise male patients with female partners of reproductive potential to use effective contraception during treatment with ZUSDURI and for 3 months following the last dose [see Use in Specific Populations (8.1, 8.3) and Clinical Pharmacology (12.1)].

6 ADVERSE REACTIONS

6.1 Clinical Trials Experience

Because clinical trials are conducted under widely varying conditions, adverse reaction rates observed in clinical trials of a drug cannot be directly compared to rates in the clinical trials of another drug and may not reflect rates observed in practice.

The safety of ZUSDURI was evaluated in ENVISION, a single-arm, multicenter study in 240 patients with recurrent LG-IR-NMIBC [see Clinical Studies (14)]. Patients received 75 mg ZUSDURI instilled once a week for 6 consecutive weeks. The median number of doses of ZUSDURI administered to patients was 6 (range 1-6) doses and 228 patients (95%) received all six scheduled doses.

Serious adverse reactions occurred in 12% of patients who received ZUSDURI, including urinary retention (0.8%) and urethral stenosis (0.4%). A fatal adverse reaction of cardiac failure occurred in 1 patient (0.4%) receiving ZUSDURI.

Permanent discontinuation of ZUSDURI due to an adverse reaction occurred in 2.9% of patients, including 1.7% who discontinued due to a renal or urinary disorder.

Dosage interruption of ZUSDURI due to adverse reactions occurred in 10% of patients. Adverse reactions (≥ 2%) which required dosage interruption were urinary tract infection (2.5%) and dysuria (2.5%).

The most common (≥ 10%) adverse reactions, including laboratory abnormalities, that occurred in patients were increased creatinine, increased potassium, dysuria, decreased hemoglobin, increased aspartate aminotransferase, increased alanine aminotransferase, increased eosinophils, decreased lymphocytes, urinary tract infection, decreased neutrophils, and hematuria.

Table 1 summarizes the adverse reactions in ENVISION.

Table 1: Adverse Reactions (≥ 10% All Grades [Graded per National Cancer Institute Common Terminology Criteria for Adverse Events (CTCAE) Version 5.0.]) in Patients Who Received ZUSDURI in ENVISION
Adverse Reaction | ZUSDURI N = 240
Adverse Reaction | All Grades (%) | Grade 3 or 4 [Only includes Grade 3 adverse reactions] (%)
Renal and urinary disorders
Dysuria | 23 | 0.4
Hematuria [Includes multiple related terms] | 10 | 0
Infections and infestations
Urinary tract infection | 12 | 0.8

Clinically relevant adverse reactions occurring in < 10% of patients receiving ZUSDURI in ENVISION included increased urinary frequency, fatigue, urinary incontinence, urinary retention, urethral stenosis, genital pain, urinary urgency, genital edema, genital pruritus, genital rash, urethritis, acute kidney injury, balanoposthitis, and nocturia.

Table 2 summarizes laboratory abnormalities in ENVISION.

Table 2: Laboratory Abnormalities (≥ 10% All Grades [Graded per National Cancer Institute Common Terminology Criteria for Adverse Events (CTCAE) Version 5.0.]) That Worsened From Baseline in Patients Who Received ZUSDURI in ENVISION
Laboratory Abnormality | ZUSDURI [The denominator used to calculate the rate varied from 227 to 238 based on the number of patients with a baseline value and at least one post-treatment value]
Laboratory Abnormality | All Grades (%) | Grade 3 or 4 [Only includes Grade 3 laboratory abnormalities] (%)
Hematology
Hemoglobin Decreased | 17 | 0.8
Eosinophils Increased | 15 | 0
Lymphocytes Decreased | 14 | 0.4
Neutrophils Decreased | 10 | 0.4
Chemistry
Creatinine Increased | 29 | 1.3
Potassium Increased | 26 | 2.2
Aspartate Aminotransferase (AST) Increased | 15 | 0.4
Alanine Aminotransferase (ALT) Increased | 15 | 0.4

8 USE IN SPECIFIC POPULATIONS

8.1 Pregnancy

Risk Summary

Based on findings in animals and mechanism of action, ZUSDURI can cause fetal harm when administered to a pregnant woman [see Clinical Pharmacology (12.1)]. There are no available data on ZUSDURI use in pregnant women to inform the drug-associated risk. In animal reproduction studies, administration of mitomycin resulted in teratogenicity (see Data). Advise pregnant women of the potential risk to a fetus.

The estimated background risk of major birth defects and miscarriage for the indicated population is unknown. In the U.S. general population, the estimated background risk of major birth defects and miscarriage in clinically recognized pregnancies is 2% - 4% and 15% - 20%, respectively.

Data

Animal Data

Teratological changes have been noted with mitomycin in animal studies.

8.2 Lactation

Risk Summary

There are no data on the presence of mitomycin in human milk, the effects on the breastfed child, or the effects on milk production. Because of the potential for serious adverse reactions in a breastfed child, advise women not to breastfeed during treatment with ZUSDURI and for 1 week following the last dose.

8.3 Females and Males of Reproductive Potential

ZUSDURI can cause fetal harm when administered to pregnant women [see Use in Specific Populations (8.1)].

Pregnancy Testing

Verify pregnancy status in females of reproductive potential prior to initiating ZUSDURI.

Contraception

Females

Advise females of reproductive potential to use effective contraception during treatment with ZUSDURI and for 6 months following the last dose.

Males

Advise male patients with female partners of reproductive potential to use effective contraception during treatment with ZUSDURI and for 3 months following the last dose.

8.4 Pediatric Use

Safety and efficacy in pediatric patients have not been established.

8.5 Geriatric Use

Of the 240 patients receiving ZUSDURI in the ENVISION study, 162 (68%) were 65 years of age and older and 89 (37%) were 75 years of age and older. No significant overall differences in safety or efficacy were observed in patients 65 years of age and older, and in patients 75 years of age and older, compared to younger patients.

8.6 Renal Impairment

Avoid use of ZUSDURI in patients with severe renal impairment (estimated glomerular filtration rate [eGFR] < 30 mL/min). A higher incidence of hematuria and urinary tract infections was observed in patients with moderate renal impairment (eGFR 30 to <60 mL/min). Monitor patients with moderate renal impairment for increased adverse reactions. No dosage adjustments are recommended in patients with mild (eGFR 60 to <90 mL/min) or moderate renal impairment.

11 DESCRIPTION

Mitomycin (also known as mitomycin-C) is an alkylating drug isolated from the broth of Streptomyces. Mitomycin is a blue-violet crystalline powder with a molecular formula of C15H18N4O5, and a molecular weight of 334.33. Its chemical name is 7-amino-9α-methoxymitosane, and it has the following structural formula:

Mitomycin is heat stable, has a high melting point, and is freely soluble in organic solvents.

ZUSDURI is supplied in a kit containing two vials of sterile lyophilized mitomycin for intravesical solution, 40 mg each, and one vial of 60 mL of sterile hydrogel, to be used as a vehicle for reconstitution.

Mitomycin for intravesical solution is a sterile, lyophilized, grey to greyish-purple, cake or powder that contains mitomycin 40 mg and mannitol 80 mg in each vial.

Hydrogel is a sterile, clear, colorless gel with or without bubbles at room temperature or clear, colorless liquid at 2°C to 8°C (36°F to 46°F), which contains 0.11 g hydroxypropyl methylcellulose, 17.12 g poloxamer, 0.63 g polyethylene glycol, and water for injection in each vial.

Once reconstituted, ZUSDURI is a clear, purple, viscous liquid at 2°C to 8°C (36°F to 46°F) or semisolid gel at room temperature, which may contain a few visible particles and have a pH between 6.0 and 8.0.

12 CLINICAL PHARMACOLOGY

12.1 Mechanism of Action

Mitomycin inhibits the synthesis of deoxyribonucleic acid (DNA). The guanine and cytosine content correlates with the degree of mitomycin-induced cross-linking. At high concentrations of the drug, cellular RNA and protein synthesis are also suppressed.

12.2 Pharmacodynamics

Mitomycin exposure-response relationships and time course of pharmacodynamic response are unknown.

12.3 Pharmacokinetics

The systemic exposure of mitomycin following instillation of 75 mg of mitomycin as ZUSDURI into the bladder was evaluated pre-instillation and hourly for up to six hours post-instillation in six patients. Mitomycin mean (range) maximum concentration (Cmax) is 2.3 ng/mL (0.2 to 8.9 ng/mL), which is less than 1% of the expected Cmax after intravenous administration.

Metabolism

Mitomycin is metabolized primarily in the liver, but metabolism occurs in other tissues as well. It is believed that the rate of clearance is inversely proportional to the maximal serum concentration because of saturation of the degradative pathways.

Excretion

Following instillation into the bladder, ZUSDURI forms a semisolid gel which dissolves in the urine. Patients reported visible gel in urine for up to 24 hours (median 5 hours) after instillation. Mitomycin is excreted unchanged in the urine. Systemically absorbed mitomycin is rapidly cleared from the serum and approximately 10% is excreted unchanged in the urine.

13 NONCLINICAL TOXICOLOGY

13.1 Carcinogenesis, Mutagenesis, Impairment of Fertility

Adequate long-term studies in animals to evaluate carcinogenic potential from instillation of mitomycin into the bladder have not been conducted. Mitomycin has been found to be carcinogenic in rats and mice. At doses approximating the recommended intravenous clinical dose in humans, mitomycin produced a greater than 100% increase in tumor incidence in male Sprague-Dawley rats, and a greater than 50% increase in tumor incidence in female Swiss mice.

The effect of ZUSDURI on fertility is unknown.

14 CLINICAL STUDIES

ENVISION Study

The efficacy of ZUSDURI was evaluated in ENVISION (NCT05243550), a single-arm, multicenter trial in 240 adults with recurrent low-grade intermediate-risk non-muscle invasive bladder cancer (LG-IR-NMIBC), of whom 223 were evaluable for response.

LG-IR-NMIBC was defined as Ta disease, histologically confirmed by biopsy, having one or two of the following: the presence of multiple tumors, a solitary tumor > 3 cm, and/or early or frequent recurrence (≥ 1 occurrence of LG-NMIBC within 1 year of the current diagnosis). Patients were required to have a previous occurrence of LG-NMIBC (Ta) treated by TURBT. The trial excluded patients with T1 tumors, or history of high-grade NMIBC within the previous two years, and/or those with prior intravesical chemotherapy within the prior two years (except for a single dose of intravesical chemotherapy immediately after any previous TURBT) and/or Bacillus Calmette-Guerin treatment within the previous year.

Patients received 75 mg ZUSDURI via urinary catheter once a week for 6 weeks.

Assessment of tumor status was performed every 3 months by cystoscopy, for-cause biopsy, and urine cytology. The major efficacy outcome measures were complete response rate (CR) at 3 months (defined as no detectable disease in the bladder by cystoscopy, biopsy [if indicated], and urine cytology) and duration of response.

The median age of patients was 70 years (range, 30-92 years); 62% were male; race was White (97.8%), Black (0.9%), Asian (0.9%), or not reported (0.4%); 1.3% were Hispanic/Latino. Multiple tumors were present in 84% of patients, 6% had a tumor > 3 cm, 55% had a previous LG-NMIBC occurrence within 1 year of the current diagnosis, and all patients had a prior TURBT for LG-NMIBC.

Efficacy results are summarized in Table 3.

Table 3: Efficacy Results in ENVISION
Efficacy Outcome Measure | ZUSDURI N = 223
Complete Response Rate % (95% CI) | 78% (72, 83)
Duration of Response [Based on observed duration of response for 173 patients who had a complete response.]
Range in months | (0.0, 25.0+)
% (n) with duration ≥ 12 months | 79% (137)
+ Denotes ongoing response.

15 REFERENCES

1. "OSHA Hazardous Drugs." OSHA. http://www.osha.gov/SLTC/hazardousdrugs/index.html

16 HOW SUPPLIED/STORAGE AND HANDLING

How Supplied

ZUSDURI is available in a kit (NDC 72493-106-03) containing the following:

- Two 40 mg (each) single-dose vials of mitomycin for intravesical solution supplied as a sterile, lyophilized, grey to greyish-purple, cake or powder. (NDC 72493-104-40)
- One single-dose vial of 60 mL sterile hydrogel supplied as a sterile, clear, colorless gel with or without bubbles at room temperature or clear, colorless liquid at 2°C to 8°C (36°F to 46°F), to be used as a vehicle for reconstitution. (NDC 72493-105-60)

Storage and Handling

Store ZUSDURI at 20°C to 25°C (68°F to 77°F); excursions permitted between 15°C and 30°C (59°F and 86°F) [see USP Controlled Room Temperature]. Avoid excessive heat over 40°C (104°F). Protect from light.

ZUSDURI is a hazardous drug. Follow applicable special handling and disposal procedures.^1

17 PATIENT COUNSELING INFORMATION

Advise the patient to read the FDA-approved patient labeling (Patient Information).

Embryo-Fetal Toxicity

Advise pregnant women and females of reproductive potential of the potential risk to a fetus. Advise females to inform their healthcare providers of a known or suspected pregnancy [see Warnings and Precautions (5.2) and Use in Specific Populations (8.1)].

Advise females of reproductive potential to use effective contraception during treatment with ZUSDURI and for 6 months following the last dose [see Use in Specific Populations (8.3)].

Advise male patients with female partners of reproductive potential to use effective contraception during treatment with ZUSDURI and for 3 months following the last dose [see Use in Specific Populations (8.3)].

Lactation

Advise women not to breastfeed during treatment with ZUSDURI and for 1 week following the last dose [see Use in Specific Populations (8.2)].

Important Post-Treatment Instructions [see Dosage and Administration (2.4)]

Advise patients that ZUSDURI contains mitomycin which is a violet to blue color and may discolor urine following the instillation procedure.

Advise patients to avoid contact with urine for at least 24 hours post-instillation [see Clinical Pharmacology (12.3)].

Advise patients to avoid urine contact with skin by voiding sitting on a toilet, flushing the toilet several times after use, and to wash hands, perineum or glans with soap and water after each instillation procedure.

Advise patients to wash clothing soiled with urine promptly and separately from other clothing.

Distributed by:
UroGen Pharma, Inc.
Princeton, NJ 08540

ZUSDURI™ is a trademark and UroGen® is a registered trademark of UroGen Pharma, Ltd.
U.S. Patent Nos. 9,040,074, 9,950,069 and 10,039,832
Copyright© 2025 UroGen Pharma, Inc.
All rights reserved.

ZUS-PI-001
PI-0017645/Ver. 1

Patient Information
ZUSDURI™ (zus-dur-ee)
(mitomycin)
for intravesical solution

What is ZUSDURI?
ZUSDURI is a prescription medicine used to treat adults with a type of cancer of the lining of the bladder called low-grade intermediate risk non-muscle invasive bladder cancer (LG-IR-NMIBC) after you have previously received bladder surgery to remove tumor and it did not work or is no longer working.
It is not known if ZUSDURI is safe and effective for use in children.

Who should not receive ZUSDURI?
Do not receive ZUSDURI if you:

- have a hole or tear (perforation) of your bladder,
- have had an allergic reaction to mitomycin or to any of the ingredients in ZUSDURI. See the end of this Patient Information leaflet for a complete list of the ingredients in ZUSDURI.

Before receiving ZUSDURI, tell your healthcare provider about all of your medical conditions, including if you:

- have kidney problems.
- are pregnant or plan to become pregnant. ZUSDURI can harm your unborn baby. You should not become pregnant during treatment with ZUSDURI. Tell your healthcare provider right away if you become pregnant or think you may be pregnant during treatment with ZUSDURI.
  Females who are able to become pregnant:
  - Your healthcare provider will check to see if you are pregnant before starting treatment with ZUSDURI.
  - You should use effective birth control (contraception) during treatment with ZUSDURI and for 6 months after the last dose.
  - Talk to your healthcare provider if you have questions about birth control options that are right for you.
  Males being treated with ZUSDURI:
  - If you have a female partner who is able to become pregnant, you should use effective birth control (contraception) during treatment with ZUSDURI and for 3 months after the last dose.
- are breastfeeding or plan to breastfeed. It is not known if ZUSDURI passes into your breast milk. Do not breastfeed during treatment with ZUSDURI and for 1 week after the last dose.

Tell your healthcare provider about all the medicines you take, including prescription and over-the-counter medicines, vitamins, and herbal supplements. Know the medicines you take. Keep a list of them to show to your healthcare provider and pharmacist when you get a new medicine.

How will I receive ZUSDURI?

- ZUSDURI will be given to you by your healthcare provider.
- You will receive ZUSDURI 1 time a week for 6 weeks into your bladder through a tube called a urinary catheter. It is important that you receive all 6 doses of ZUSDURI according to your healthcare provider's instructions.
- If you miss any appointments, call your healthcare provider as soon as possible to reschedule your appointment.
- During treatment with ZUSDURI, your healthcare provider may tell you to take additional medicines or change how you take your current medicines. Ask your healthcare provider if you have any questions.

After receiving ZUSDURI:

- ZUSDURI may cause your urine color to change to a violet to blue color.
- Avoid contact between your skin and urine for at least 24 hours.
- To urinate, males and females should sit on a toilet and flush the toilet several times after you use it.
- After going to the bathroom, wash your hands, your inner thighs, and genital area well with soap and water.
- Clothing that comes in contact with urine should be washed right away and washed separately from other clothing.

What are the possible side effects of ZUSDURI?

The most common side effects of ZUSDURI include:

- increased blood creatinine levels
- increased blood potassium levels
- trouble with urination
- decreased red blood cell counts

- increase in certain blood liver tests
- increased or decreased white blood cell counts
- urinary tract infection
- blood in your urine

Call your doctor for medical advice about possible side effects. You may report side effects to FDA at 1-800-FDA-1088.
You can also report side effects to UroGen Pharma at 1-855-987-6436.

General information about ZUSDURI.
Medicines are sometimes prescribed for purposes other than those listed in this Patient Information leaflet. You can ask your pharmacist or healthcare provider for information about ZUSDURI that is written for healthcare professionals.

What are the ingredients of ZUSDURI?
Active ingredient: mitomycin
Inactive ingredients: hydroxypropyl methylcellulose, mannitol, poloxamer, polyethylene glycol, and water for injection
Distributed by: UroGen Pharma, Inc., Princeton, NJ 08540
ZUSDURI™ is a trademark and UroGen® is a registered trademark of UroGen Pharma, Ltd.
U.S. Patent Nos. 9,040,074, 9,950,069 and 10,039,832
Copyright© 2025 UroGen Pharma, Inc.
All rights reserved.
For more information go to www.ZUSDURI.com or call 1-855-987-6436.

This Patient Information has been approved by the U.S. Food and Drug Administration.

Issued: 06/2025

ZUS-PPI-001

INSTRUCTIONS FOR PHARMACY (IFP) ZUSDURI™ (zus-dur-ee) (mitomycin) for intravesical solution

Purpose of this Instructions for Pharmacy

This Instructions for Pharmacy contains information on how to prepare ZUSDURI using pharmacy supplies and a Chilling Block or other means of chilling.

Intended Use of ZUSDURI

ZUSDURI (mitomycin) for intravesical solution is indicated for the treatment of adult patients with recurrent low-grade intermediate risk non-muscle invasive bladder cancer (LG-IR-NMIBC).

Important Information You Need to Know Before Reconstituting ZUSDURI

Reconstituted ZUSDURI must be prepared under chilled conditions. ZUSDURI cannot be prepared without a Chilling Block or other means of chilling.

Once reconstituted with sterile hydrogel, ZUSDURI will appear as a semisolid gel under room temperature conditions and as a viscous liquid under chilled conditions.

Preparation of ZUSDURI must be performed under aseptic conditions.

Storage Conditions and Handling

Before reconstitution, store ZUSDURI at room temperature, 20°C to 25°C (68°F to 77°F). Excursions are permitted between 15°C and 30°C (59°F and 86°F). Avoid excessive heat over 40°C (104°F). Protect from light.

Storage Instructions for Reconstituted ZUSDURI:

- Instill reconstituted ZUSDURI as soon as possible.
- If not used immediately, store reconstituted ZUSDURI:
  - under refrigeration at 2℃ to 8℃ (36°F to 46°F) for up to 7 days; or
  - under refrigeration at 2℃ to 8℃ (36°F to 46°F) for up to 6 days followed by no more than 24 hours at room temperature, 20°C to 25°C (68°F to 77°F).
- Discard 7 days after reconstitution.
- Protect from light.
- Avoid excessive heat over 40°C (104°F).

ZUSDURI is a hazardous drug. Procedures for Proper Handling and Disposal of hazardous drugs should be followed.

Supplies Needed

ZUSDURI available in a kit containing:

- Two vials of ZUSDURI, 40 mg per vial
- One vial of Sterile hydrogel, 60 mL
- One ZUSDURI admixture label
- ZUSDURI Prescribing Information (PI)
- ZUSDURI Instructions for Pharmacy (IFP)
- ZUSDURI Instructions for Administration (IFA)

Pharmacy Supplies:

(Provided by your facility)

Do not substitute any of these components

Two 20 mL Luer lock syringes

Two 5 mL Luer lock syringes filled with 3 mL sterile water

Three OnGuard®2 CSTD vial adaptors

Four OnGuard®2 CSTD syringe adaptors

Chilling Block or other means of chilling (device design may vary)
Note: The day before the preparation, place the Chilling Block in the freezer at -20°C to -12°C (-4°F to 10.4°F). Refer to the Chilling Block Instructions for Use for more information.

Steps to Prepare ZUSDURI Admixture

A. Freeze the Chilling Block
  1. The day before preparation, put the Chilling Block in the freezer at -20°C to -12°C (-4°F to 10.4°F).
    Note: Please refer to the Chilling Block Instructions for Use for additional information.

B. Prepare Supplies
  1. Remove the Chilling Block from the freezer.
  2. Disinfect the Chilling Block as per your pharmacy's policy. Allow it to air dry, and then place it inside the hood or isolator.
  3. Connect vial adaptors to all three vials.
  4. Connect syringe adaptors to both empty 20 mL syringes and both sterile water syringes.
  5. Place one ZUSDURI vial, the sterile hydrogel vial, and both empty 20 mL syringes in the Chilling Block for approximately 20 minutes.
    Note: The Chilling Block has five compartments, but only four are needed. The small vial compartment will not be used during this preparation.

  6. Set the second ZUSDURI vial and both sterile water syringes aside for later use.

C. Reconstitute the First ZUSDURI Vial
  1. Slowly fill one chilled 20 mL syringe with 14 mL of sterile hydrogel.
  2. Slowly fill the other chilled 20 mL syringe with 13 mL of sterile hydrogel.
  3. Place both 20 mL syringes and the sterile hydrogel vial back in the Chilling Block.
  4. Remove the chilled ZUSDURI vial from the Chilling Block.
  5. Inject 3 mL of sterile water into the ZUSDURI vial.
  6. Gently swirl the ZUSDURI vial upright at least 20 times.
    Note: Do not invert or shake the vial.
  7. Inject the chilled 14 mL and 13 mL syringes of sterile hydrogel into the ZUSDURI vial.
  8. Place both empty 20 mL syringes back in the Chilling Block for later use.
  9. Vigorously swirl the ZUSDURI vial upright for about 2 minutes.
    Note: Do not invert or shake the vial.
  10. Set the first ZUSDURI vial aside for later use.

D. Reconstitute the Second ZUSDURI Vial
  1. Place the second ZUSDURI vial in the Chilling Block.
  2. Slowly fill one chilled 20 mL syringe with 14 mL of sterile hydrogel.
  3. Slowly fill the other chilled 20 mL syringe with 13 mL of sterile hydrogel.
  4. Place both 20 mL syringes back in the Chilling Block.
  5. Discard the empty sterile hydrogel vial.
  6. Remove the chilled ZUSDURI Vial from the Chilling Block.
  7. Inject 3 mL of sterile water into the ZUSDURI vial.
  8. Gently swirl the ZUSDURI vial upright at least 20 times.
    Note: Do not invert or shake the vial.
  9. Inject the chilled 14 mL and 13 mL syringes of sterile hydrogel into the ZUSDURI vial.
  10. Place both empty 20 mL syringes back in the Chilling Block for later use.
  11. Vigorously swirl the ZUSDURI vial upright for about 2 minutes.
    Note: Do not invert or shake the vial.

E. Combine the Contents of the ZUSDURI Admixture Vials
  1. Slowly fill each chilled 20 mL syringe with 14 mL of admixture from the second ZUSDURI vial (for a total of 28 mL).
    Note: If you are having difficulty withdrawing the admixture, place the components back in the Chilling Block until the admixture liquifies again.
  2. Inject the two 14 mL admixture syringes into the first ZUSDURI vial.
  3. You now have one vial that contains ZUSDURI admixture.

F. Dispense Reconstituted ZUSDURI
  1. Write the "Discard after" date and time on the supplied admixture label and apply to the prepared ZUSDURI admixture vial. You may also substitute your pharmacy's label for dispensing the ZUSDURI admixture.
    Note: The "Discard after" date and time is 7 days from the completion of the preparation. Store reconstituted ZUSDURI at 2°C to 8°C (36°F to 46°F) for up to 7 days. Alternatively, reconstituted ZUSDURI may be stored under refrigeration at 2℃ to 8℃ (36°F to 46°F) for up to 6 days followed by no more than 24 hours at room temperature, 20°C to 25°C (68°F to 77°F). Avoid excessive heat over 40°C (104°F). Protect from light.
  2. Transport the following items to the treatment facility:
    i. One reconstituted ZUSDURI vial.
    ii. ZUSDURI Instructions for Administration (IFA).

Important to Remember

- All components need to be kept cold during the preparation process by placing them in the Chilling Block or other means of chilling when they are not in use.
- If you are having difficulty pushing or withdrawing the solution at any time, place the components back in the Chilling Block or other means of chilling until the product liquifies again.

Frequently Asked Questions

How do I connect the vial adaptor?
Place the vial adaptor over the vial and press down firmly. You will hear a snap which confirms successful attachment.

How do I connect the syringe adaptor?
Screw the Luer lock end of the syringe adaptor onto the syringe hub until it is finger tight.

How do I connect the syringe adaptor to the vial adaptor?
Place the syringe adaptor over the vial adaptor and align the tabs, then press down firmly. You will hear a snap which confirms successful attachment.

How do I disconnect the syringe adaptor from the vial adaptor?
Pinch the tabs on the syringe adaptor to separate it from the vial adaptor.

Do I have to keep the vials upright when mixing? If so, why?
Yes, the vials should be kept upright when mixing to ensure the contents are fully mixed at the bottom of the vial.

I am having difficulty working with the drug product. It seems to be solidifying.
If you are having difficulty pushing or withdrawing the solution, place the components back in the Chilling Block or other means of chilling until it liquifies.

This Instructions for Pharmacy has been approved by the U.S. Food and Drug Administration.

Distributed by:
UroGen Pharma, Inc.
Princeton, NJ 08540
www.ZUSDURI.com

ZUSDURI™ is a trademark of UroGen Pharma, Ltd.
OnGuard® is a registered trademark of Simplivia Healthcare, Ltd.

Copyright© 2025 UroGen Pharma, Inc.
All rights reserved.

ZUS-IFP-001
IFP-0017643/Ver. 1

INSTRUCTIONS FOR ADMINISTRATION (IFA) ZUSDURI™ (zus-dur-ee) (mitomycin) for intravesical solution For Intravesical Instillation Only

Read and follow this Instructions for Administration prior to each ZUSDURI instillation.

Purpose of this Instructions for Administration

This Instructions for Administration contains information on how to instill ZUSDURI using the ZUSDURI vial and the devices listed under Supplies Needed, obtained by your facility.

Intended Use of ZUSDURI

ZUSDURI (mitomycin) for intravesical solution is indicated for the treatment of adult patients with recurrent low-grade intermediate risk non-muscle invasive bladder cancer (LG-IR-NMIBC).

Important Information You Need to Know Before Instilling ZUSDURI

ZUSDURI must be reconstituted by a healthcare professional prior to instillation. Reconstituted ZUSDURI will appear as a semisolid gel. Once chilled, ZUSDURI will convert to a viscous liquid for instillation.

Once instilled into the patient's bladder, ZUSDURI will convert to a semisolid gel, thereby exposing the lining of the bladder to mitomycin over a prolonged period of time.

Storage Instructions for Reconstituted ZUSDURI:

- Instill reconstituted ZUSDURI as soon as possible.
- If not used immediately, store reconstituted ZUSDURI:
  - under refrigeration at 2℃ to 8℃ (36°F to 46°F) for up to 7 days; or
  - under refrigeration at 2℃ to 8℃ (36°F to 46°F) for up to 6 days followed by no more than 24 hours at room temperature, 20°C to 25°C (68°F to 77°F).
- Discard 7 days after reconstitution.
- Protect from light.
- Avoid excessive heat over 40°C (104°F).

When ready to instill, chill ZUSDURI at -3°C to 5°C (27°F to 41°F) for about 20 minutes to revert it to a viscous liquid. See Steps A through C below for complete administration instructions.

ZUSDURI is a hazardous drug. Procedures for proper handling and disposal of hazardous drugs should be followed, as described below.

Supplies Needed

One vial of reconstituted ZUSDURI, with resultant concentration of 80 mg per 60 mL.
(prepared and provided by your pharmacy)

Ice Bath
Note: The ice bath should consist of ice and cold water and be large enough to submerge a ZUSDURI vial.

Plastic Bag

Ancillary Supplies

When you administer ZUSDURI, you will need to use special adaptors for your catheter and syringes. These adaptors will create a closed pathway to protect you and your patient during and after administration. Fluid will only be able to pass between connection points when the adaptors are fully engaged, preventing drips or leaks.

Once the adaptors are connected, do not disconnect them. They are there for your protection.

Urinary Catheter
One 12 Fr to 16 Fr with fixed Luer lock connector

Do not substitute

Catheter Adaptor
One OnGuard®2 CSTD Luer lock adaptor

Do not substitute

Administration Syringes
Four 20 mL polypropylene Luer lock syringes (BD Luer-Lok™ Syringe)

Do not substitute

Sterile Water Flush
One 5 mL Luer lock syringe filled with 3 mL sterile water

Syringe Adaptors
Five OnGuard®2 CSTD syringe adaptors

Do not substitute

Instillation Instructions

A. Chill the ZUSDURI
  1. Place the ZUSDURI vial in a plastic bag.
  2. Place the plastic bag in the ice bath for approximately 20 minutes.
    Note: Ensure the ZUSDURI vial is completely immersed in the ice bath.
B. Prepare the Four Administration Syringes
  1. Connect a syringe adaptor to the 3 mL sterile water syringe and set aside.
  2. Connect syringe adaptors to the four 20 mL syringes. These will be the administration syringes.
    Note: Once the adaptors are connected, do not disconnect them. They are there for your protection.
  3. Remove the ZUSDURI vial from the ice bath and verify the admixture is liquid. If the admixture is not liquid, place the vial bag back into the ice bath until the admixture liquefies.
  4. Swirl the vial upright to ensure that ZUSDURI is uniformly mixed.
  5. Slowly fill each of the four administration syringes with 14 mL of ZUSDURI admixture (for a total of 56 mL).
    Note: there might be foaming in the syringe while withdrawing ZUSDURI.
  6. Place the four administration syringes in the plastic bag.
  7. Place the plastic bag in the ice bath, ensuring the four administration syringes are completely immersed, for at least two minutes.
C. Instill ZUSDURI
  The contents of four administration syringes must be instilled in rapid succession without delay to avoid ZUSDURI solidification. Before proceeding:
  - Ensure that all four administration syringes contain liquid ZUSDURI.
  - Keep all four administration syringes chilled in the ice bath until instillation time.
  1. Place the urinary catheter in the bladder and drain the urine.
  2. Connect the catheter adaptor to the urinary catheter.
  3. Connect an administration syringe to the urinary catheter.
  4. Instill the ZUSDURI into the patient.
    Note: Empty each administration syringe over approximately 30 seconds. ZUSDURI is viscous, even in a chilled state.
  5. Disconnect the syringe adaptor from the catheter adaptor.
  6. Immediately repeat these steps without delay for the remaining three administration syringes.
  7. After all four administration syringes have been instilled, flush the urinary catheter with 3 mL of sterile water.
  8. Wait 15 minutes before removing the urinary catheter from the patient.
  9. Discard all ancillary supplies according to your facility's procedures for hazardous waste.

Frequently Asked Questions

How do I connect the syringe adaptor?
Screw the Luer lock end of the syringe adaptor onto the syringe hub until it is finger tight.

How do I connect the syringe adaptor to the vial adaptor?
Place the syringe adaptor over the vial adaptor and align the tabs; then press down firmly. You will hear a snap which confirms successful attachment.

How do I disconnect the syringe adaptor from the vial adaptor?
Pinch the tabs on the syringe adaptor to separate it from the vial adaptor.

I am having a hard time working with ZUSDURI. It seems to be solidifying.
If you are having difficulty pushing or withdrawing ZUSDURI, recap and place the components back into the ice bath until ZUSDURI liquifies. The vial may be placed upside down within the bag in the ice bath.

How do I connect the catheter adaptor to the urinary catheter?
Screw the Luer lock end of the catheter adaptor onto the urinary catheter connector until it is finger tight.

How do I connect the syringe adaptor to the catheter adaptor?
Place the syringe adaptor in front of the catheter adaptor and push it on firmly. You will hear a snap which confirms successful attachment.

How do I disconnect the syringe adaptor from the catheter adaptor?
While holding the urinary catheter steady and fixed in its position, pinch the tabs on the syringe adaptor to separate it from the catheter adaptor.

This "Instructions for Administration" has been approved by the U.S. Food and Drug Administration.

Distributed by:

UroGen Pharma, Inc.
Princeton, NJ 08540
www.ZUSDURI.com

ZUSDURI™ is a trademark of UroGen Pharma, Ltd.
OnGuard® is a registered trademark of Simplivia Healthcare Ltd.
BD Luer-Lok™ is a trademark of Becton, Dickinson and Company.

Copyright© 2025 UroGen Pharma, Inc.
All rights reserved.

ZUS-IFA-001
IFA-0017644/Ver. 1

PRINCIPAL DISPLAY PANEL - 40 mg Kit Carton

NDC 72493-106-03

Zusduri™
(mitomycin) for intravesical solution
40 mg per Vial

Attention Pharmacist: Reconstitution
is required prior to dispensing.
See the Instructions for Pharmacy
before proceeding.

SINGLE-DOSE KIT
Warning: For Intravesical Use Only

Rx Only

Contents of Kit:

- 2 Single-Dose Vials of ZUSDURI (mitomycin) for intravesical solution, 40 mg per Vial.
- 1 Single-Dose Vial of Sterile Hydrogel, 60 mL per Vial
- 1 Admixture Label
- Full Prescribing Information
- Instructions for Pharmacy
- Instructions for Administration

Store at 20°C to 25°C (68°F to 77°F); excursions permitted between 15°C and 30°C (59°F and 86°F).
Avoid excessive heat over 40°C (104°F). Protect from light.
Store reconstituted ZUSDURI at 2°C to 8°C (36°F to 46°F) for up to 7 days.
Alternatively, reconstituted ZUSDURI may be stored under refrigeration at 2°C to 8°C (36°F to 46°F)
for up to 6 days followed by no more than 24 hours at room temperature, 20°C to 25°C (68°F to 77°F).
Avoid excessive heat over 40°C (104°F).
Protect reconstituted ZUSDURI from light.
When ready to instill, chill ZUSDURI at -3°C to 5°C (27°F to 41°F) for about 20 minutes to revert it to a
viscous liquid.

Recommended Dosage: See Full Prescribing Information.

Warning: Hazardous Drug

Distributed by:
UroGen Pharma, Inc.
Princeton, NJ 08540

UroGen®
Pharma

PRINCIPAL DISPLAY PANEL - 40 mg Vial Label

NDC 72493-104-40

Single-Dose Vial
Sterile

Zusduri™
(mitomycin) for intravesical solution
40 mg per Vial

See Instructions for Pharmacy for preparation instructions
Must be Reconstituted with Sterile Hydrogel Before Use

Warning: For Intravesical Use Only

Store at 20°C to 25°C (68°F to 77°F); excursions permitted between 15°C and 30°C
(59°F and 86°F). Avoid excessive heat over 40°C (104°F). Protect from light.
Each vial contains: Mitomycin 40 mg and mannitol 80 mg.

Recommended Dosage: See Full Prescribing Information.

Distributed by:
UroGen Pharma, Inc.
Princeton, NJ 08540

Lot
Exp

Warning: Hazardous Drug
Rx Only

UroGen®
Pharma

620565

LBL-0017642/Ver. 1

PRINCIPAL DISPLAY PANEL - 60 mL Vial Label

NDC 72493-105-60
Single-Dose Vial

Sterile Hydrogel

For use in preparation of ZUSDURI™
(mitomycin) for intravesical solution

Not for Direct Administration

See Instructions for Pharmacy for
preparation instructions

Store at 20°C to 25°C (68°F to 77°F); excursions
permitted between 15°C and 30°C (59°F and 86°F).
Avoid excessive heat over 40°C (104°F).

Rx Only

60 mL per Vial

LBL-0017641/Ver. 1